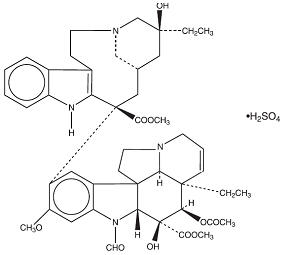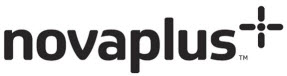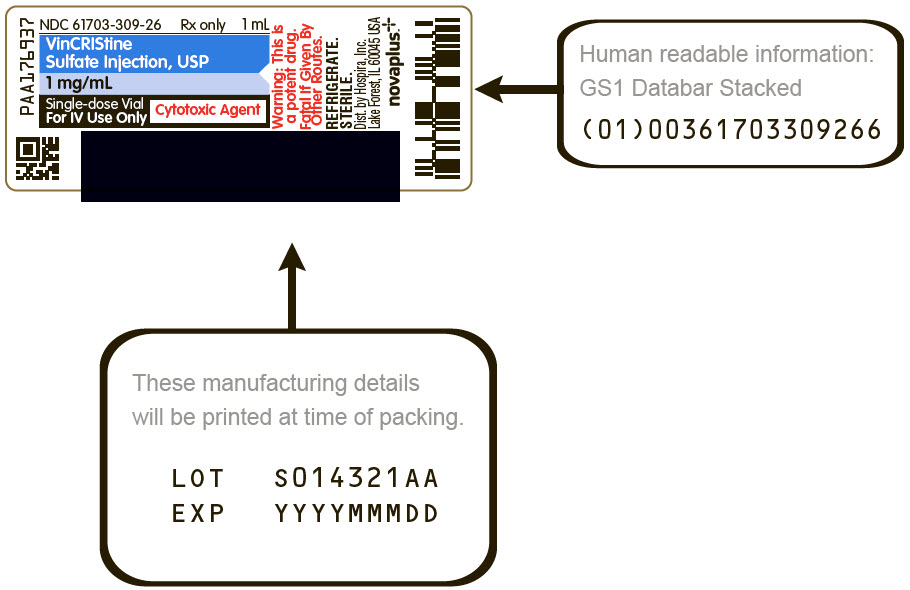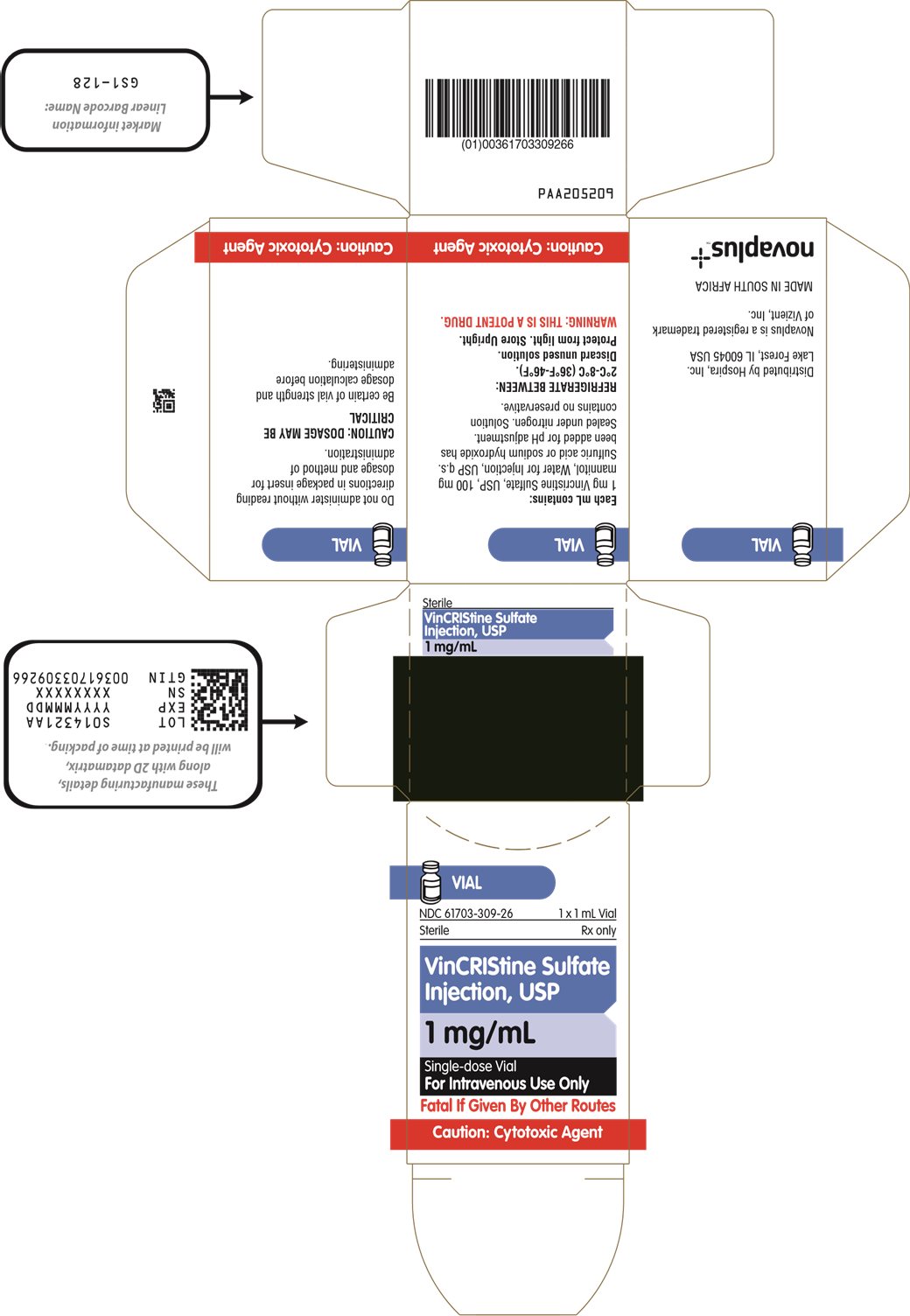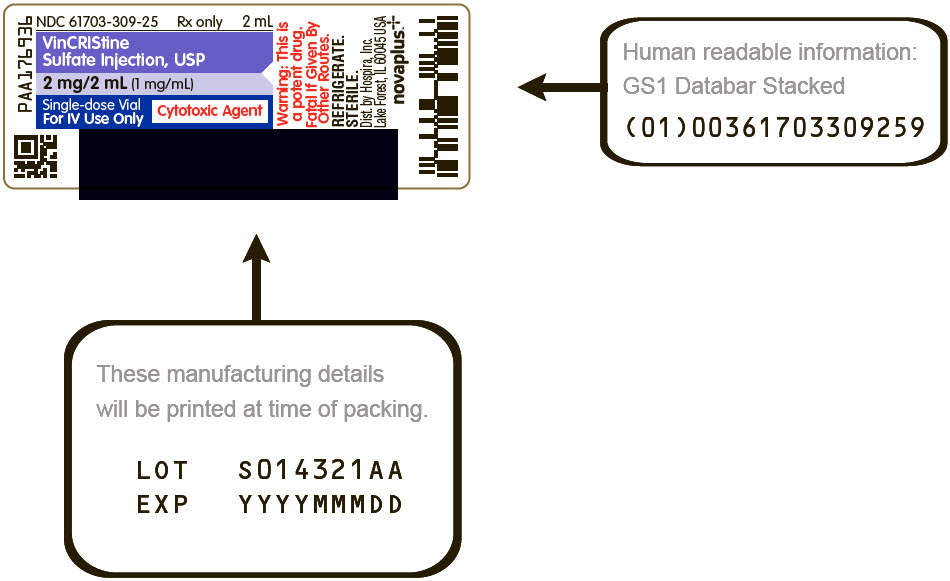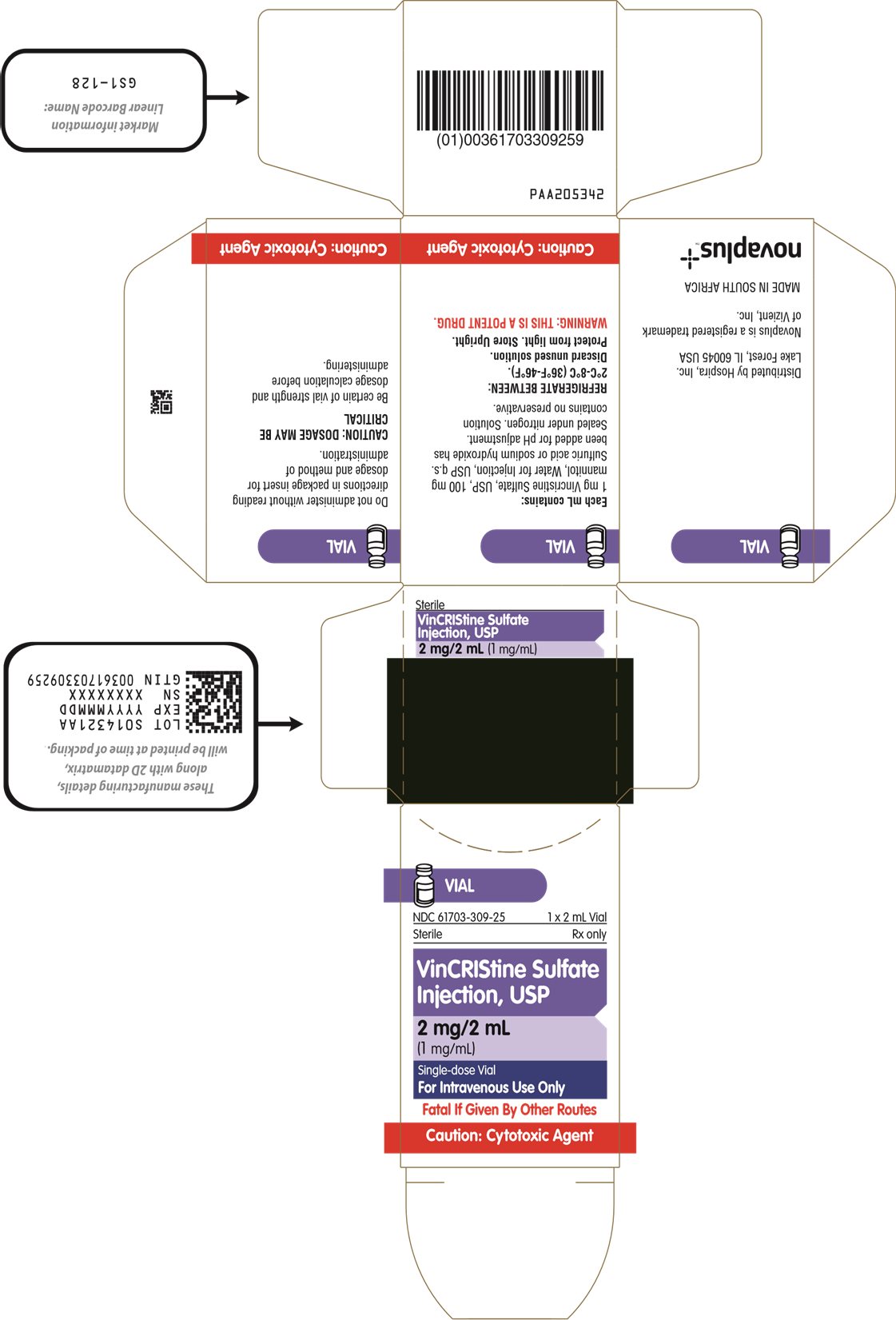 DRUG LABEL: VinCRIStine Sulfate
NDC: 61703-309 | Form: INJECTION, SOLUTION
Manufacturer: Hospira, Inc.
Category: prescription | Type: HUMAN PRESCRIPTION DRUG LABEL
Date: 20260217

ACTIVE INGREDIENTS: VINCRISTINE SULFATE 1 mg/1 mL
INACTIVE INGREDIENTS: MANNITOL 100 mg/1 mL; SULFURIC ACID; SODIUM HYDROXIDE; WATER

VinCRIStine Sulfate
Injection, USP

Rx only

PRESERVATIVE FREE SOLUTION

WARNINGS

Caution–This preparation should be administered by individuals experienced in the administration of Vincristine Sulfate Injection. It is extremely important that the intravenous needle or catheter be properly positioned before any vincristine is injected. Leakage into surrounding tissue during intravenous administration of Vincristine Sulfate Injection may cause considerable irritation. If extravasation occurs, the injection should be discontinued immediately, and any remaining portion of the dose should then be introduced into another vein. Local injection of hyaluronidase and the application of moderate heat to the area of leakage help disperse the drug and are thought to minimize discomfort and the possibility of cellulitis.

FOR INTRAVENOUS USE ONLY – FATAL IF GIVEN BY OTHER ROUTES.

See OVERDOSAGE section for the treatment of patients given intrathecal Vincristine Sulfate Injection.

DESCRIPTION

Vincristine Sulfate Injection, USP is the salt of an alkaloid obtained from a common flowering herb, the periwinkle plant (Vinca rosea Linn). Originally known as leurocristine, it has also been referred to as LCR and VCR.

The molecular formula for Vincristine Sulfate, USP is C46H56N4O10∙H2SO4. It has a molecular weight of 923.04.

The structural formula is as follows:

Vincristine Sulfate, USP is a white to off–white powder. It is soluble in methanol, freely soluble in water, but only slightly soluble in 95% ethanol. In 98% ethanol, Vincristine Sulfate, USP has an ultraviolet spectrum with maxima at 221 nm (ϵ+47,100).

Vincristine Sulfate Injection, USP is a sterile, preservative–free, single-dose only solution available for intravenous use in 1 mg/mL and 2 mg/2 mL (1 mg/mL) vials. Each mL contains 1 mg Vincristine Sulfate, USP, 100 mg mannitol and Water for Injection, USP. Q.S. Sulfuric acid or sodium hydroxide have been added for pH control. The pH of Vincristine Sulfate Injection, USP ranges from 4.0 to 5.0. At the time of manufacture, the air in the containers is replaced by nitrogen.

CLINICAL PHARMACOLOGY

The mechanisms of action of vincristine sulfate remain under investigation. The mechanism of action of vincristine sulfate has been related to the inhibition of microtubule formation in mitotic spindle, resulting in an arrest of dividing cells at the metaphase stage.

Central nervous system leukemia has been reported in patients undergoing otherwise successful therapy with vincristine sulfate. This suggests that vincristine does not penetrate well into the cerebrospinal fluid.

Pharmacokinetic studies in patients with cancer have shown a triphasic serum decay pattern following rapid intravenous injection. The initial, middle and terminal half–lives are 5 minutes, 2.3 hours, and 85 hours respectively; however, the range of the terminal half–life in humans is from 19 to 155 hours. The liver is the major excretory organ in humans and animals. The metabolism of vinca alkaloids has been shown to be mediated by hepatic cytochrome P450 isoenzymes in the CYP 3A subfamily. This metabolic pathway may be impaired in patients with hepatic dysfunction or who are taking concomitant potent inhibitors of these isoenzymes (see PRECAUTIONS). About 80% of an injected dose of vincristine sulfate appears in the feces and 10% to 20% can be found in the urine. Within 15 to 30 minutes after injection, over 90% of the drug is distributed from the blood into tissue, where it remains tightly, but not irreversibly, bound.

Current principles of cancer chemotherapy involve the simultaneous use of several agents. Generally, each agent used has a unique toxicity and mechanism of action so that therapeutic enhancement occurs without additive toxicity. It is rarely possible to achieve equally good results with single–agent methods of treatment. Thus, vincristine sulfate is often chosen as part of polychemotherapy because of lack of significant bone–marrow suppression (at recommended doses) and of unique clinical toxicity (neuropathy). See DOSAGE AND ADMINISTRATION section for possible increased toxicity when used in combination therapy.

INDICATIONS AND USAGE

Vincristine Sulfate Injection is indicated in acute leukemia.

Vincristine Sulfate Injection has also been shown to be useful in combination with other oncolytic agents in Hodgkin's disease, non–Hodgkin's malignant lymphomas, rhabdomyosarcoma, neuroblastoma, and Wilms' tumor.

CONTRAINDICATIONS

Patients with the demyelinating form of Charcot–Marie–Tooth syndrome should not be given Vincristine Sulfate Injection. Careful attention should be given to those conditions listed under WARNINGS and PRECAUTIONS.

WARNINGS

WARNINGS

This preparation is for intravenous use only. It should be administered by individuals experienced in the administration of Vincristine Sulfate Injection. The intrathecal administration of Vincristine Sulfate Injection usually results in death.

To reduce the potential for fatal medication errors due to incorrect route of administration, Vincristine Sulfate Injection should be diluted in a flexible plastic container and prominently labeled as indicated "FOR INTRAVENOUS USE ONLY – FATAL IF GIVEN BY OTHER ROUTES."

See OVERDOSAGE section for the treatment of patients given intrathecal Vincristine Sulfate Injection.

Pregnancy

Vincristine sulfate can cause fetal harm when administered to a pregnant woman. When pregnant mice and hamsters were given doses of vincristine sulfate that caused resorption of 23% to 85% of fetuses, fetal malformations were produced in those that survived. Five monkeys were given single doses of vincristine sulfate between days 27 and 34 of their pregnancies; 3 of the fetuses were normal at term, and 2 viable fetuses had grossly evident malformations at term. In several animal species, vincristine sulfate can induce teratogenesis as well as embryo death at doses that are nontoxic to the pregnant animal. There are no adequate and well–controlled studies in pregnant women. If this drug is used during pregnancy or if the patient becomes pregnant while receiving this drug, she should be apprised of the potential hazard to the fetus. Women of child–bearing potential should be advised to avoid becoming pregnant.

PRECAUTIONS

General

Acute uric acid nephropathy, which may occur after the administration of oncolytic agents, has also been reported with vincristine sulfate. In the presence of leukopenia or a complicating infection, administration of the next dose of Vincristine Sulfate Injection warrants careful consideration. Treatment with vincristine sulfate in combination with other chemotherapy agents may cause myelosuppression. Monitor complete blood counts during treatment with vincristine sulfate (see Laboratory Tests below) and provide supportive care, including administration of hematopoietic growth factors, as clinically indicated.

If central nervous system leukemia is diagnosed, additional agents may be required, because vincristine does not appear to cross the blood–brain barrier in adequate amounts.

Particular attention should be given to dosage and neurologic side effects if Vincristine Sulfate Injection is administered to patients with preexisting neuromuscular disease and when other drugs with neurotoxic potential are also being used.

Acute shortness of breath and severe bronchospasm have been reported following the administration of vinca alkaloids. These reactions have been encountered most frequently when the vinca alkaloid was used in combination with mitomycin–C and may require aggressive treatment, particularly when there is preexisting pulmonary dysfunction. The onset of these reactions may occur minutes to several hours after the vinca alkaloid is injected and may occur up to 2 weeks following the dose of mitomycin. Progressive dyspnea requiring chronic therapy may occur. Vincristine sulfate should not be readministered.

Care must be taken to avoid contamination of the eye with concentration of Vincristine Sulfate Injection used clinically. If accidental contamination occurs severe irritation (or, if the drug was delivered under pressure, even corneal ulceration) may result. The eye should be washed immediately and thoroughly.

The safety of immunization with live vaccines during treatment with vincristine sulfate has not been studied and vaccination with a live virus is not recommended during treatment with vincristine sulfate. Follow current vaccination practice guidelines for administration of live vaccines for patients who have received chemotherapy after completion of treatment with vincristine sulfate.

Laboratory Tests

Because dose–limiting clinical toxicity is manifested as neurotoxicity clinical evaluation (e.g., history, physical examination) is necessary to detect the need for dosage modification. Following administration of Vincristine Sulfate Injection, some individuals may have a fall in the white blood cell count or platelet count, particularly when previous therapy or the disease itself has reduced bone–marrow function. Therefore, a complete blood count should be done before administration of each dose. Acute elevation of serum uric acid may also occur during induction of remission in acute leukemia; thus, such levels should be determined frequently during the first 3 to 4 weeks of treatment or appropriate measures taken to prevent uric acid nephropathy. The laboratory performing these tests should be consulted for its range of normal values.

Drug Interactions

The simultaneous oral or intravenous administration of phenytoin and antineoplastic chemotherapy combinations that included vincristine sulfate has been reported to reduce blood levels of the anticonvulsant and to increase seizure activity. Dosage adjustment should be based on serial blood level monitoring. The contribution of vincristine sulfate to this interaction is not certain. The interaction may result from reduced absorption of phenytoin and an increase in the rate of its metabolism and elimination.

Vincristine sulfate is a substrate for cytochrome P450 3A isozymes (CYP3A). Concurrent administration of vincristine sulfate with itraconazole or fluconazole (known inhibitors of the CYP3A metabolic pathway) has been reported to cause an earlier onset and/or an increased severity of neuromuscular side effects (see ADVERSE REACTIONS). This interaction is presumed to be related to inhibition of the metabolism of vincristine. Therefore, the concomitant use of strong CYP3A inhibitors with vincristine sulfate should be avoided. Patients should be frequently monitored for adverse reactions with concomitant use of moderate CYP3A inhibitors (e.g., fluconazole) with vincristine sulfate.

Concurrent use of strong CYP3A inducers (e.g., St. John's Wort) with vincristine sulfate should be avoided.

Vincristine sulfate is also a substrate for P-glycoprotein (P-gp). Therefore, the concomitant use of P-gp inhibitors or inducers should be avoided.

Carcinogenesis, Mutagenesis, Impairment of Fertility

Neither in vivo nor in vitro laboratory tests have conclusively demonstrated the mutagenicity of this product. Fertility following treatment with vincristine sulfate alone for malignant disease has not been studied in humans. Clinical reports of both male and female patients who received multiple–agent chemotherapy that included vincristine sulfate indicate that azoospermia and amenorrhea can occur in postpubertal patients. Recovery occurred many months after completion of chemotherapy in some but not all patients. When the same treatment is administered to prepubertal patients, permanent azoospermia and amenorrhea are much less likely.

Patients who received chemotherapy with vincristine sulfate in combination with anti–cancer drugs known to be carcinogenic have developed second malignancies. The contributing role of vincristine sulfate in this development has not been determined. No evidence of carcinogenicity was found following intraperitoneal administration of vincristine sulfate in rats and mice, although this study was limited.

Usage in Pregnancy

See WARNINGS.

Nursing Mothers

It is not known whether this drug is excreted in human milk. Because many drugs are excreted in human milk and because of the potential for serious adverse reactions due to vincristine sulfate in nursing infants, a decision should be made either to discontinue nursing or the drug, taking into account the importance of the drug to the mother.

Pediatric Use

See DOSAGE AND ADMINISTRATION section.

ADVERSE REACTIONS

Prior to the use of this drug, patients and/or their parents/guardian should be advised of the possibility of untoward symptoms.

In general, adverse reactions are reversible and are related to dosage. The most common adverse reaction is hair loss; the most troublesome adverse reactions are neuromuscular in origin.

When single, weekly doses of the drug are employed, the adverse reactions of leukopenia, neuritic pain, and constipation occur but are usually of short duration (ie., less than 7 days). When the dosage is reduced, these reactions may lessen or disappear. The severity of such reactions seems to increase when the calculated amount of drug is given in divided doses. Other adverse reactions, such as hair loss, sensory loss, paresthesia, difficulty in walking, slapping gait, loss of deep–tendon reflexes, and muscle wasting, may persist for at least as long as therapy is continued. Generalized sensorimotor dysfunction may become progressively more severe with continued treatment. Although most such symptoms usually disappear by about the sixth week after discontinuance of treatment, some neuromuscular difficulties may persist for prolonged periods in some patients. Regrowth of hair may occur while maintenance therapy continues.

The following adverse reactions have been reported:

Hepatic veno-occlusive disease has been reported in patients receiving vincristine, particularly in pediatric patients, as part of standard combination chemotherapy regimens. Some of the patients had fatal outcomes; some who survived had undergone liver transplantation.

Hypersensitivity

Rare cases of allergic–type reactions, such as anaphylaxis, rash and edema, that are temporally related to vincristine therapy have been reported in patients receiving vincristine as a part of multidrug chemotherapy regimens.

Gastrointestinal

Constipation, abdominal cramps, weight loss, nausea, vomiting, oral ulceration, diarrhea, paralytic ileus, intestinal necrosis and/or perforation, and anorexia have occurred. Constipation may take the form of upper–colon impaction, and, on physical examination, the rectum may be empty. Colicky abdominal pain coupled with an empty rectum may mislead the physician. A flat film of the abdomen is useful in demonstrating this condition. All cases have responded to high enemas and laxatives. A routine prophylactic regimen against constipation is recommended for all patients receiving Vincristine Sulfate Injection.

Paralytic ileus (which mimics the "surgical abdomen") may occur, particularly in young pediatric patients. The ileus will reverse itself with temporary discontinuance of Vincristine Sulfate Injection and with symptomatic care.

Genitourinary

Polyuria, dysuria, and urinary retention due to bladder atony have occurred. Other drugs known to cause urinary retention (particularly in the elderly) should, if possible, be discontinued for the first few days following administration of Vincristine Sulfate Injection.

Cardiovascular

Hypertension and hypotension have occurred. Chemotherapy combinations that have included vincristine sulfate, when given to patients previously treated with mediastinal radiation, have been associated with coronary artery disease and myocardial infarction. Causality has not been established.

Neurologic

Frequently, there is a sequence to the development of neuromuscular side effects. Initially, only sensory impairment and paresthesia may be encountered. With continued treatment, neuritic pain and, later, motor difficulties may occur. There have been no reports of any agent that can reverse the neuromuscular manifestations that may accompany therapy with vincristine sulfate.

Loss of deep–tendon reflexes, foot drop, ataxia, and paralysis have been reported with continued administration. Cranial nerve manifestations, such as isolated paresis and/or paralysis of muscles controlled by cranial motor nerves including potentially life–threatening bilateral vocal cord paralysis, may occur in the absence of motor impairment elsewhere; extraocular and laryngeal muscles are those most commonly involved. Jaw pain, pharyngeal pain, parotid gland pain, bone pain, back pain, limb pain, and myalgias have been reported; pain in these areas may be severe. Convulsions, frequently with hypertension, have been reported in a few patients receiving vincristine sulfate. Several instances of convulsions followed by coma have been reported in pediatric patients. Transient cortical blindness and optic atrophy with blindness have been reported. Treatment with vinca alkaloids has resulted in both vestibular and auditory damage to the eighth cranial nerve. Manifestations include partial or total deafness which may be temporary or permanent, and difficulties with balance including dizziness, nystagmus, and vertigo. Particular caution is warranted when vincristine is used in combination with other agents known to be ototoxic such as the platinum–containing oncolytics.

Pulmonary

See PRECAUTIONS section. Acute respiratory distress syndrome has been reported.

Endocrine

Rare occurrences of a syndrome attributable to inappropriate antidiuretic hormone secretion have been observed in patients treated with vincristine sulfate. This syndrome is characterized by high urinary sodium excretion in the presence of hyponatremia; renal or adrenal disease, hypotension, dehydration, azotemia, and clinical edema are absent. With fluid deprivation, improvement occurs in the hyponatremia and in the renal loss of sodium.

Hematologic

Vincristine Sulfate Injection does not appear to have any constant or significant effect on platelets or red blood cells. Serious bone–marrow depression is usually not a major dose–limiting event. However, anemia, leukopenia, and thrombocytopenia have been reported. Thrombocytopenia, if present when therapy with Vincristine Sulfate Injection is begun, may actually improve before the appearance of bone marrow remission. Granulocytopenia has been reported.

Skin

Alopecia and rash have been reported.

Other

Fever, headache, dehydration, and hyperuricemia have occurred.

OVERDOSAGE

Side effects following the use of Vincristine Sulfate Injection are dose related. In pediatric patients under 13 years of age, death has occurred following doses of vincristine sulfate that were 10 times those recommended for therapy. Severe symptoms may occur in this patient group following dosages of 3 to 4 mg/m^2. Adults can be expected to experience severe symptoms after single doses of 3 mg/m^2 or more (see ADVERSE REACTIONS). Therefore, following administration of doses higher than those recommended, patients can be expected to experience exaggerated side effects. Supportive care should include the following: (1) prevention of side effects resulting from the syndrome of inappropriate antidiuretic hormone secretion (preventive treatment would include restriction of fluid intake and perhaps the administration of a diuretic affecting the function of Henle's loop and the distal tubule); (2) administration of anticonvulsants; (3) use of enemas or cathartics to prevent ileus (in some instances, decompression of the gastrointestinal tract may be necessary); (4) monitoring the cardiovascular system; (5) determining daily blood counts for guidance in transfusion requirements.

Folinic acid has been observed to have a protective effect in normal mice that were administered lethal doses of vincristine sulfate (Cancer Res 1963;23:1390). Isolated case reports suggest that folinic acid may be helpful in treating humans who have received an overdose of vincristine sulfate. It is suggested that 100 mg of folinic acid be administered intravenously every 3 hours for 24 hours and then every 6 hours for at least 48 hours. Theoretically (based on pharmacokinetic data), tissue levels of vincristine sulfate can be expected to remain significantly elevated for at least 72 hours. Treatment with folinic acid does not eliminate the need for the above mentioned supportive measures.

Most of an intravenous dose of vincristine is excreted into the bile after rapid tissue binding (see CLINICAL PHARMACOLOGY). Because only very small amounts of the drug appear in dialysate, hemodialysis is not likely to be helpful in cases of overdosage. An increase in the severity of side effects may be experienced by patients with liver disease that is severe enough to decrease biliary excretion. Enhanced fecal excretion of parenterally administered vincristine has been demonstrated in dogs pretreated with cholestyramine. There are no published clinical data on the use of cholestyramine as an antidote in humans.

There are no published clinical data on the consequences of oral ingestion of vincristine. Should oral ingestion occur, the stomach should be evacuated. Evacuation should be followed by oral administration of activated charcoal and a cathartic.

Treatment of patients following intrathecal administration of Vincristine Sulfate Injection has included immediate removal of spinal fluid and flushing with Lactated Ringer's, as well as other solutions and has not prevented ascending paralysis and death. In one case, progressive paralysis in an adult was arrested by the following treatment initiated immediately after the intrathecal injection:

1. As much spinal fluid was removed as could be safely done through lumbar access.
2. The subarachnoid space was flushed with Lactated Ringer's solution infused continuously through a catheter in a cerebral lateral ventricle at the rate of 150 mL/h. The fluid was removed through a lumbar access.
3. As soon as fresh frozen plasma became available, the fresh frozen plasma, 25 mL, diluted in 1 L of Lactated Ringer's solution was infused through the cerebral ventricular catheter at the rate of 75 mL/h with removal through the lumbar access. The rate of infusion was adjusted to maintain a protein level in the spinal fluid of 150 mg/dL.
4. Glutamic acid, 10 g, was given intravenously over 24 hours followed by 500 mg 3 times daily by mouth for 1 month or until neurological dysfunction stabilized. The role of glutamic acid in this treatment is not certain and may not be essential.

DOSAGE AND ADMINISTRATION

This preparation is for intravenous use only (see WARNINGS).

Neurotoxicity appears to be dose related. Extreme care must be used in calculating and administering the dose of Vincristine Sulfate Injection since overdosage may have a very serious or fatal outcome.

The usual dose of Vincristine Sulfate Injection for pediatric patients is 1.5–2 mg/m^2. For pediatric patients weighing 10 kg or less, the starting dose should be 0.05 mg/kg, administered once a week. The usual dose of Vincristine Sulfate Injection for adults is 1.4 mg/m^2. A 50% reduction in the dose of Vincristine Sulfate Injection is recommended for patients having a direct serum bilirubin value above 3 mg/100 mL.

The drug is administered intravenously at weekly intervals.

TO REDUCE THE POTENTIAL FOR FATAL MEDICATION ERRORS DUE TO INCORRECT ROUTE OF ADMINISTRATION, VINCRISTINE SULFATE INJECTION SHOULD BE DILUTED IN A FLEXIBLE PLASTIC CONTAINER AND PROMINENTLY LABELED AS INDICATED FOR INTRAVENOUS USE ONLY – FATAL IF GIVEN BY OTHER ROUTES (See WARNINGS).

The concentration of Vincristine Sulfate Injection is 1 mg/mL. Do not add extra fluid to the vial prior to removal of the dose. Withdraw the solution of Vincristine Sulfate Injection into an accurate dry syringe, measuring the dose carefully. Do not add extra fluid to the vial in an attempt to empty it completely.

Preparation for flexible plastic container

Vincristine Sulfate Injection when diluted with 0.9% Sodium Chloride Injection in concentrations from 0.0015 mg/mL to 0.08 mg/mL is stable for up to 24 hours when protected from light or 8 hours under normal light at 25°C.

Caution: It is extremely important that the intravenous needle or catheter be properly positioned before any vincristine is injected. Leakage into surrounding tissue during intravenous administration of Vincristine Sulfate Injection may cause considerable irritation. If extravasation occurs, the injection should be discontinued immediately and any remaining portion of the dose should then be introduced into another vein. Local injection of hyaluronidase and the application of moderate heat to the area of leakage will help disperse the drug and may minimize discomfort and the possibility of cellulitis.

Vincristine Sulfate Injection must be administered via an intact, free–flowing intravenous needle or catheter. Care should be taken that there is no leakage or swelling occurring during administration (see boxed WARNINGS).

The diluted Vincristine Sulfate Injection may be infused via a flexible plastic container directly into an intravenous catheter/needle or into a running intravenous infusion (see Drug Interactions below).

Patients Receiving Radiation Therapy

Vincristine Sulfate Injection should not be given to patients while they are receiving radiation therapy through ports that include the liver. When Vincristine Sulfate Injection is used in combination with L–asparaginase, Vincristine Sulfate Injection should be given 12 to 24 hours before administration of the enzyme in order to minimize toxicity; administering L–asparaginase before Vincristine Sulfate Injection may reduce hepatic clearance of vincristine.

Drug Interactions

Vincristine Sulfate Injection should not be diluted in solutions that raise or lower the pH outside the range of 3.5 to 5.5. It should not be mixed with anything other than 0.9% Sodium Chloride Injection USP.

Whenever solution and container permit, parenteral drug products should be inspected visually for particulate matter and discoloration prior to administration.

Handling and Disposal

Procedures for proper handling and disposal of anticancer drugs should be considered. Several guidelines on this subject have been published.^1 There is no general agreement that all of the procedures recommended in the guidelines are necessary or appropriate.

HOW SUPPLIED

Vincristine Sulfate Injection, USP, is available as follows:

Unit of Sale | Total Strength/Total Volume; (Concentration)
NDC 61703–309–26; Carton of 1 single-dose flip-top vial (blue cap) | 1 mg/mL
NDC 61703–309–25; Carton of 1 single-dose flip-top vial (blue cap) | 2 mg/2 mL; (1 mg/mL)

STORAGE AND HANDLING

This product should be refrigerated between 2°C–8°C (36°F–46°F). Discard unused solution. Protect from light. Store Upright.

REFERENCES

1. OSHA Hazardous Drugs. OSHA. http://www.osha.gov/SLTC/hazardousdrugs/index.html

Distributed by: Hospira, Inc. Lake Forest, IL 60045 USA

Novaplus is a registered trademark of Vizient, Inc.

LAB-1313-8.0

Revised: 12/2025

PRINCIPAL DISPLAY PANEL - 1 mL Vial Label

NDC 61703-309-26
Rx only
1 mL

VinCRIStine
Sulfate Injection, USP

1 mg/mL

Single-dose Vial
For IV Use Only

Cytotoxic Agent

PRINCIPAL DISPLAY PANEL - 1 mL Vial Carton

VIAL

NDC 61703-309-26
1 x 1 mL Vial

Sterile
Rx only

VinCRIStine Sulfate
Injection, USP

1 mg/mL

Single-dose Vial
For Intravenous Use Only

Fatal If Given By Other Routes

Caution: Cytotoxic Agent

PRINCIPAL DISPLAY PANEL - 2 mL Vial Label

NDC 61703-309-25
Rx only
2 mL

VinCRIStine
Sulfate Injection, USP

2 mg/2 mL (1 mg/mL)

Single-dose Vial
For IV Use Only

Cytotoxic Agent

PRINCIPAL DISPLAY PANEL - 2 mL Vial Carton

VIAL

NDC 61703-309-25
1 x 2 mL Vial

Sterile
Rx only

VinCRIStine Sulfate
Injection, USP

2 mg/2 mL
(1 mg/mL)

Single-dose Vial
For Intravenous Use Only

Fatal If Given By Other Routes

Caution: Cytotoxic Agent